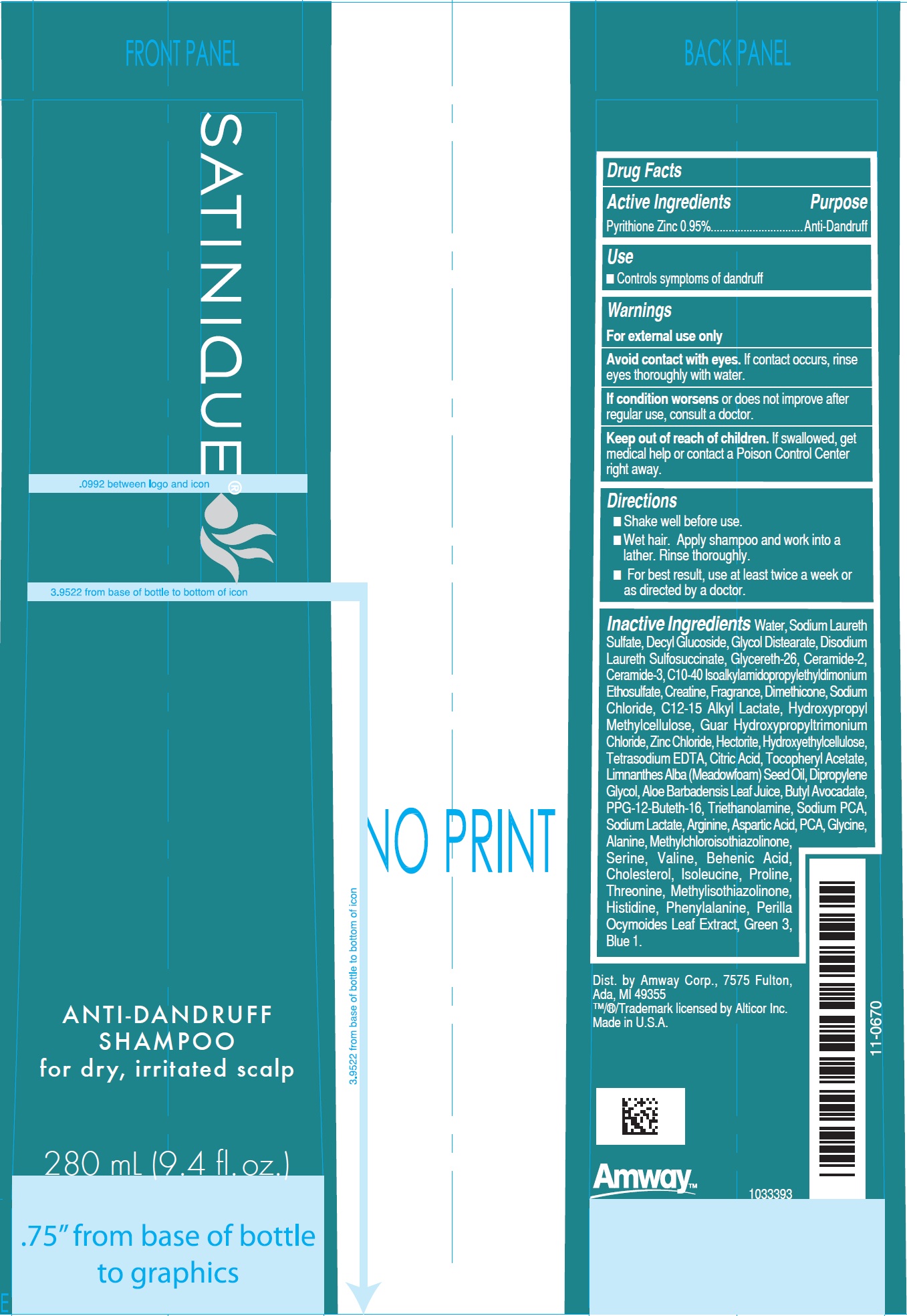 DRUG LABEL: Satinique Anti Dandruff
NDC: 10056-006 | Form: CREAM
Manufacturer: Access Business Group LLC
Category: otc | Type: HUMAN OTC DRUG LABEL
Date: 20231023

ACTIVE INGREDIENTS: PYRITHIONE ZINC 9.5 mg/1 mL
INACTIVE INGREDIENTS: WATER; SODIUM LAURETH-3 SULFATE; DECYL GLUCOSIDE; GLYCOL DISTEARATE; DISODIUM LAURETH SULFOSUCCINATE; GLYCERETH-26; CERAMIDE 2; CERAMIDE 3; CREATINE; DIMETHICONE; SODIUM CHLORIDE; C12-15 ALKYL LACTATE; HYPROMELLOSES; GUAR HYDROXYPROPYLTRIMONIUM CHLORIDE (1.7 SUBSTITUENTS PER SACCHARIDE); ZINC CHLORIDE; HECTORITE; EDETATE SODIUM; CITRIC ACID MONOHYDRATE; .ALPHA.-TOCOPHEROL ACETATE; MEADOWFOAM SEED OIL; PROPYLENE GLYCOL; ALOE VERA LEAF; PPG-12-BUTETH-16; TROLAMINE; SODIUM PYRROLIDONE CARBOXYLATE; SODIUM LACTATE; ARGININE; ASPARTIC ACID; PIDOLIC ACID; GLYCINE; ALANINE; METHYLCHLOROISOTHIAZOLINONE; SERINE; VALINE; BEHENIC ACID; CHOLESTEROL; ISOLEUCINE; PROLINE; THREONINE; METHYLISOTHIAZOLINONE; HISTIDINE; PHENYLALANINE; PERILLA FRUTESCENS LEAF; FD&C GREEN NO. 3; FD&C BLUE NO. 1

Satinique Anti-Dandruff shampoo

Active Ingredients

Pyrithione Zinc 0.95%

Purpose

Anti Dandruff

Uses

- Controls symptoms of dandruff

Warnings

For external use only.

If contact occurs, rinse eyes thoroughly with water. Avoid contact with eyes.

or does not improve after regular use, consult a doctor. If condition worsens

Keep out of reach of children.

If swallowed, get medical help or contact a Poison Control Center right away.

Directions

- Shake well before use.
- Wet hair. Apply shampoo and work into a lather. Rinse thoroughly.
- For best result, use at least twice a week or as directed by a doctor.

Inactive Ingredients

Water, Sodium Laureth Sulfate, Decyl Glucoside, Glycol Distearate, Disodium Laureth Sulfosuccinate, Glycereth-26, Ceramide 2 , Ceramide-3, C10-40 isoalkylamidopropylethyldimonium ethosulfate, Creatine, Fragrance, Dimethicome, Sodium Chloride, C12-15 Alkyl Lactate, Hydroxypropyl Methylcellulose, Guar Hydroxypropyltrimonium Chloride, Zinc Chloride, Hectorite, Hydroxyethylcellulose, Tetrasodium EDTA, Citric Acid, Tocopheryl Acetate, Limnanthes Alba (Meadowfoam) Seed Oil, Propylene Glycol, Aloe Barbadensis Leaf Juice, Butyl Avodate, PPG-12-Buteth-15, Triethanolamine, Sodium PCA, Sodium Lactate, Arginine, Aspartic Acid, PCA, Glycine, Alanine, MethylChlororisothiazolinone, Serine, Valine, Behenic Acid, Cholesterol, Isoleucine, Proline, Threonine, Methylisothiazolinone, Histidine, Phenylalanine, Perilla Ocymoides Leaf Extract, Green 3, Blue 1.